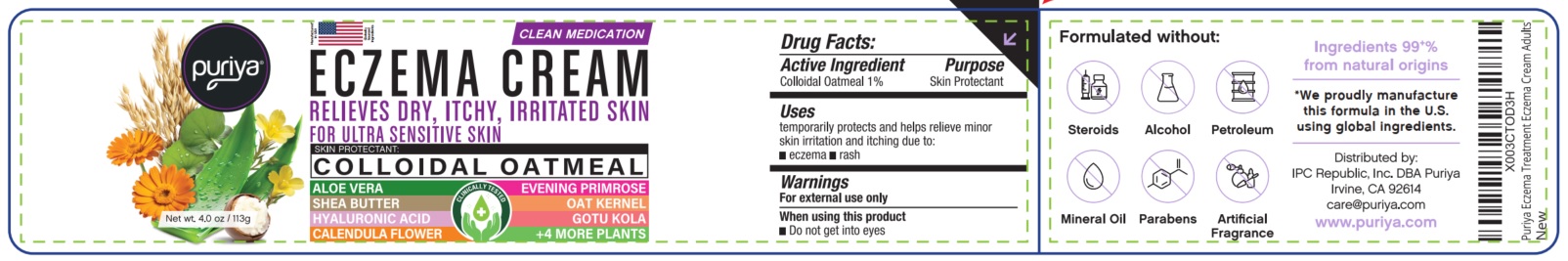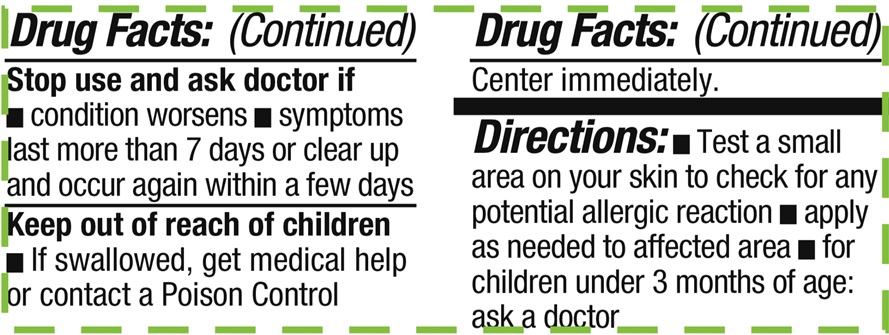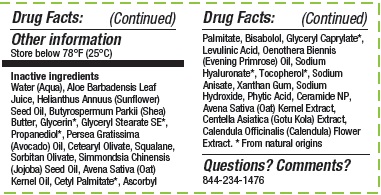 DRUG LABEL: Puriya Eczema Cream
NDC: 84711-002 | Form: CREAM
Manufacturer: IPC Republic, Inc.
Category: otc | Type: HUMAN OTC DRUG LABEL
Date: 20260101

ACTIVE INGREDIENTS: OATMEAL 1 g/100 g
INACTIVE INGREDIENTS: EVENING PRIMROSE OIL; XANTHAN GUM; ALOE VERA LEAF; AVOCADO OIL; SUNFLOWER OIL; HYALURONATE SODIUM; TOCOPHEROL; GLYCERYL CAPRYLATE; LEVULINIC ACID; SORBITAN OLIVATE; GLYCERIN; JOJOBA OIL; CALENDULA OFFICINALIS FLOWER; ASCORBYL PALMITATE; SODIUM ANISATE; OAT; SQUALANE; SODIUM HYDROXIDE; CERAMIDE NP; WATER; CETEARYL OLIVATE; CETYL PALMITATE; GLYCERYL STEARATE SE; PROPANEDIOL; SHEA BUTTER; OAT KERNEL OIL; LEVOMENOL; FYTIC ACID; CENTELLA ASIATICA LEAF

Puriya Eczema Cream

Active ingredient

Colloidal Oatmeal 1%

Purpose
Skin Protectant

Uses
temporarily protects and helps relieve minor
skin irritation and itching due to:
•eczema •rash

Warnings
For external use only

When using this product
•Do not get into eyes

Stop use and ask doctor if •condition worsens •symptoms last more than 7 days or clear up and occur again within a few days

Keep out of reach of children •If swallowed, get medical help or contact a Poison Control Center immediately.

DOSAGE AND ADMINISTRATION

Directions: •Test a small area on your skin to check for any potential allergic reaction •apply as needed to affected area •for children under 3 months of age: ask a doctor

Inactive ingredients
Water (Aqua), Aloe Barbadensis Leaf Juice, Helianthus Annuus (Sunower) Seed Oil, Butyrospermum Parkii (Shea) Butter, Glycerin*, Glyceryl Stearate SE*, Propanediol*, Persea Gratissima (Avocado) Oil, Cetearyl Olivate, Squalane, Sorbitan Olivate, Simmondsia Chinensis (Jojoba) Seed Oil, Avena Sativa (Oat) Kernel Oil, Cetyl Palmitate*, Ascorbyl Palmitate, Bisabolol, Glyceryl Caprylate*, Levulinic Acid, Oenothera Biennis (Evening Primrose) Oil, Sodium Hyaluronate*, Tocopherol*, Sodium Anisate, Xanthan Gum, Sodium Hydroxide, Phytic Acid, Ceramide NP, Avena Sativa (Oat) Kernel Extract, Centella Asiatica (Gotu Kola) Extract, Calendula Officinalis (Calendula) Flower Extract. *From natural origins

Other information

Store below 78°F (25°C)

Questions? Comments?
844-234-1476

Distributed by:
IPC Republic, Inc. DBA Puriya
Irvine, CA 92614
care@puriya.com
www.puriya.com

Made in USA
from domestic and
global sources

PACKAGE LABEL

puriya®

ECZEMA CREAM

RELIEVES DRY, ITCHY, IRRITATED SKIN
FOR ULTRA SENSITIVE SKIN

SKIN PROTECTANT:

COLLOIDAL OATMEAL

ALOE VERA EVENING PRIMPROSE

SHEA BUTTER OAT KERNEL

HYALURONIC ACID GOTU KOLA

CALENDULA FLOWER +4 MORE PLANTS

Net wt. 4.0 oz / 113g